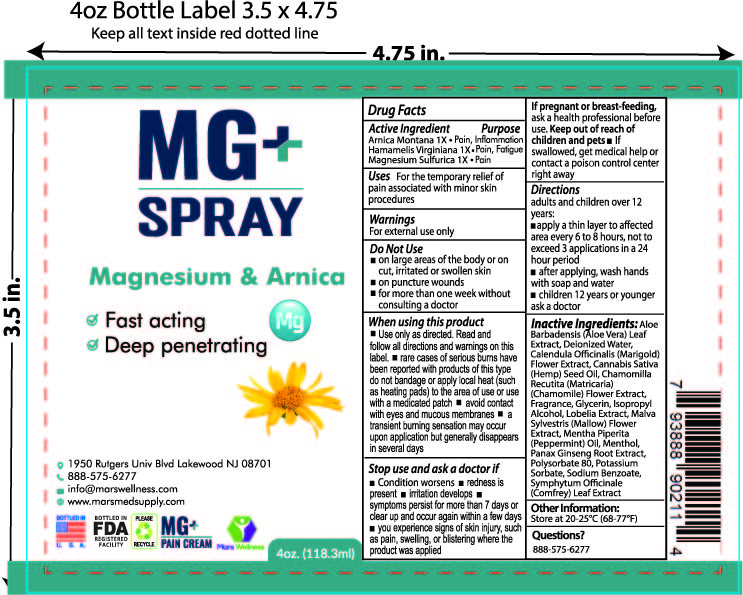 DRUG LABEL: MARS WELLNESS MAGNESIUM
NDC: 76348-810 | Form: SPRAY
Manufacturer: RENU LABORATORIES, LLC
Category: homeopathic | Type: HUMAN OTC DRUG LABEL
Date: 20250514

ACTIVE INGREDIENTS: WITCH HAZEL 0.11 g/112 g; ARNICA MONTANA 1.12 g/112 g; MAGNESIUM SULFATE, UNSPECIFIED 0.12 g/112 g
INACTIVE INGREDIENTS: WATER; PEPPERMINT OIL; POLYSORBATE 80; MENTHOL; MALVA SYLVESTRIS FLOWER; CANNABIS SATIVA SEED OIL; POTASSIUM SORBATE; ISOPROPYL ALCOHOL; SODIUM BENZOATE; LOBELIA INFLATA; ALOE VERA LEAF; COMFREY LEAF; CALENDULA OFFICINALIS FLOWER; CHAMOMILE; PANAX GINSENG FLOWER

MARS WELLNESS MAGNESIUM PLUS SPRAY

ACTIVE INGREDIENT

Arnica Montana 1X

Hamamelis Virginiana 1X

Magnesium Sulfurica 1X

PURPOSE

Inflammation

Pain, Fatigue

Pain

INDICATIONS AND USAGE

For the temporary relief of pain associated with minor skin procedures

WARNINGS

For external use only.

Do Not Use

- on large areas of the body or on cut, irritated or swollen skin
- on puncture wounds
- for more than one week without consulting a doctor

When using this product

- Use only as directed. Read and follow all directions and warnings on this label.
- rare cases of serious burns have been reported with products of this type. Do not bandage or apply local heat (such as heating pads) to the area of use or use with a medicated patch
- avoid contact with eyes and mucous membranes
- a transient burning sensation may occur upon application but generally disappears in several days

Stop use and ask a doctor if

- Condition worsens
- redness is present
- Irritation develops
- symptoms persist for more than 7 days or clear up and occur again within a few days.
- you experience signs of skin injury, such as pain, swelling, or blistering where the product was applied.

If pregnant or breast-feeding,

ask a health professional before use. Keep out of reach of children and pets.

- If swallowed, get medical help or contact a poison control center right away.

Keep out of reach of children and pets.

Directions

adults and children over 12 years:

- apply a thin layer to affected area every 6 to 8 hours, not to exceed 3 applications in a 24 hour period
- after applying, wash hands with soap and water
- children 12 years or younger, ask a doctor

No major changes - this is a new listing

Inactive Ingredients:

Aloe Barbadensis (Aloe Vera) Leaf Extract, Deionized Water, Calendula Officinalis (Marigold) Flower Extract, Cannabis Sativa (Hemp) Seed Oil, Chamomilla Recutita (Matricaria) (Chamomile) Flower Extract, Fragrance, Glycerin, Isopropyl Alcohol, Lobelia Extract, Malva Sylvestris (Mallow) Flower Extract, Mentha piperita (Peppermint) Oil, Menthol, Panax Ginseng Root Extract, Polysorbate 80, Potassium Sorbate, Sodium Benzoate, Symphytum Officinale (Comfrey) Leaf Extract

STORAGE AND HANDLING

Store at 20 - 25 degrees C (68 - 77 degrees F)

Questions ?

888-575-6277

Bottle label